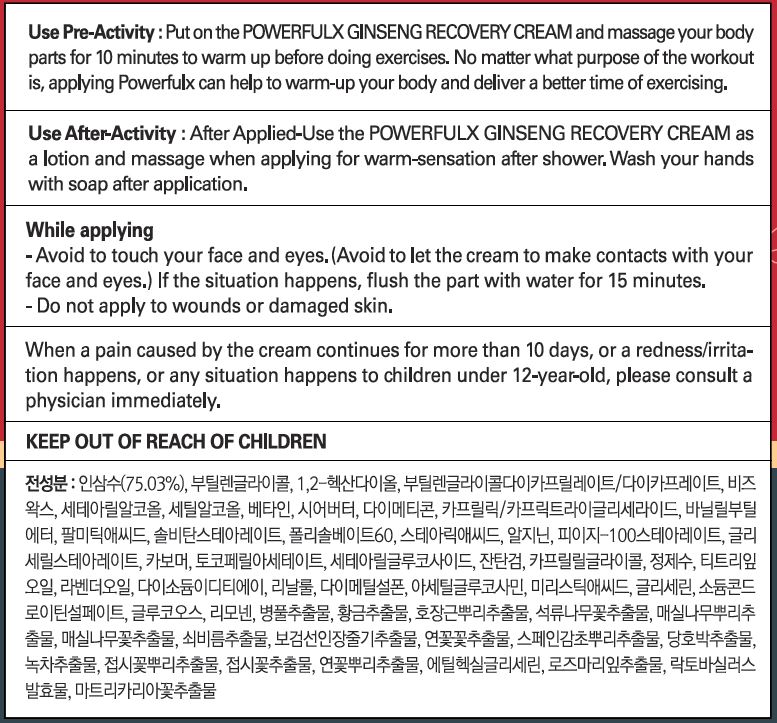 DRUG LABEL: Powerfulx Ginseng RecoveryCream
NDC: 70042-0004 | Form: CREAM
Manufacturer: Power Fulx Co., Ltd.
Category: otc | Type: HUMAN OTC DRUG LABEL
Date: 20250109

ACTIVE INGREDIENTS: DIMETHYL SULFONE 0.1 g/100 mL; N-ACETYLGLUCOSAMINE 0.15 g/100 mL; PANAX GINSENG ROOT WATER 66.2186 g/100 mL
INACTIVE INGREDIENTS: WATER

Drug Facts

ACTIVE INGREDIENT

Panax Ginseng Root Water, Acetyl Glucosamine, Dimethyl Sulfone, Sodium Chondroitin Sulfate

INACTIVE INGREDIENT

Water, etc

PURPOSE

Effection : Recovery and pain relief of minor aches and pains of muscles and joints

keep out of reach of the children

WARNINGS

Warnings : For external use only: avoiding the face and eye areas.

DOSAGE AND ADMINISTRATION

for external use only

Directions :

ㆍApply a proper amount of this product to skin 10 minutes before exercise.

ㆍAfter shower, apply to skin and massage.